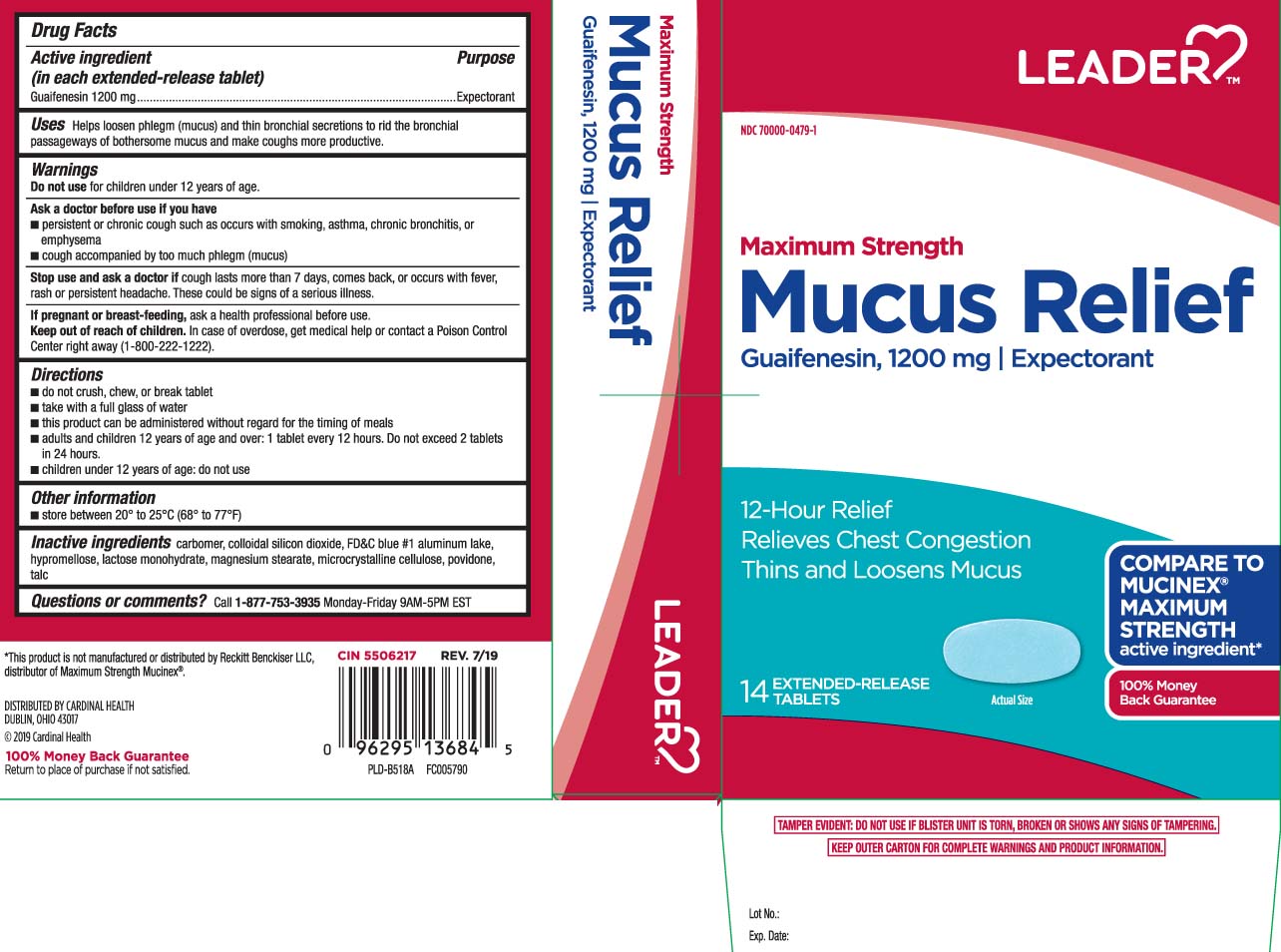 DRUG LABEL: Mucus Relief Extended Release
NDC: 70000-0479 | Form: TABLET
Manufacturer: CARDINAL HEALTH 110, LLC. DBA LEADER 70000
Category: otc | Type: HUMAN OTC DRUG LABEL
Date: 20260210

ACTIVE INGREDIENTS: GUAIFENESIN 1200 mg/1 1
INACTIVE INGREDIENTS: SILICON DIOXIDE; MAGNESIUM STEARATE; CARBOMER 934; CELLULOSE, MICROCRYSTALLINE; POVIDONE; FD&C BLUE NO. 1; HYPROMELLOSE, UNSPECIFIED; LACTOSE MONOHYDRATE; TALC

Drug Facts

Active ingredient (in each extended-release tablet)

Guaifenesin 1200 mg

Purpose

Expectorant

Uses

Helps loosen phlegm (mucus) and thin bronchial secretions to rid the bronchial passageways of bothersome mucus and makes coughs more productive.

Warnings

Do not use

for children under 12 years of age.

Ask a doctor before use if you have

- persistent or chronic cough such as occurs with smoking, asthma, chronic bronchitis or emphysema
- cough accompanied by too much phlegm (mucus)

Stop use and ask a doctor if

cough lasts more than 7 days, comes back, or occurs with fever, rash or persistent headache. These could be signs of a serious illness.

If pregnant or breast-feeding,

ask a health professional before use.

Keep out of reach of children.

In case of overdose, get medical help or contact a Poison Control Center right away (1-800-222-1222).

Directions

- do not crush, chew, or break tablet
- take with a full glass of water
- this product can be administered without regard for the timing of meals
- adults and children 12 years of age and over: 1 tablet every 12 hours. Do not exceed 2 tablets in 24 hours.
- children under 12 years of age: do not use

Other information

- store between 20º to 25ºC (68º to 77ºF)

Inactive ingredients

carbomer, colloidal silicon dioxide, FD&C blue #1 aluminum lake, hypromellose, lactose monohydrate, magnesium stearate, microcrystalline cellulose, povidone, talc

Questions or comments?

Call 1-877-753-3935 Monday-Friday 9AM-5PM EST

Principal Display Panel

COMPARE TO MUCINEX® MAXIMUM STRENGTH active ingredient*

Maximum Strength

Mucus Relief

Guaifenesin, 1200 mg | Expectorant

12-Hour Relief

Relieves Chest Congestion

Thins and Loosens Mucus

EXTENDED-RELEASE TABLETS

*This product is not manufactured or distributed by Reckitt Benckiser LLC, distributor of Maximum Strength Mucinex®.

TAMPER EVIDENT: DO NOT USE IF BLISTER UNIT IS TORN, BROKEN OR SHOWS ANY SIGNS OF TAMPERING.

KEEP OUTER CARTON FOR COMPLETE WARNINGS AND PRODUCT INFORMATION.

DISTRIBUTED BY CARDINAL HEALTH

DUBLIN OHIO 43017

www.myleader.com

Package Label

LEADER Maximum Strength Mucus Relief